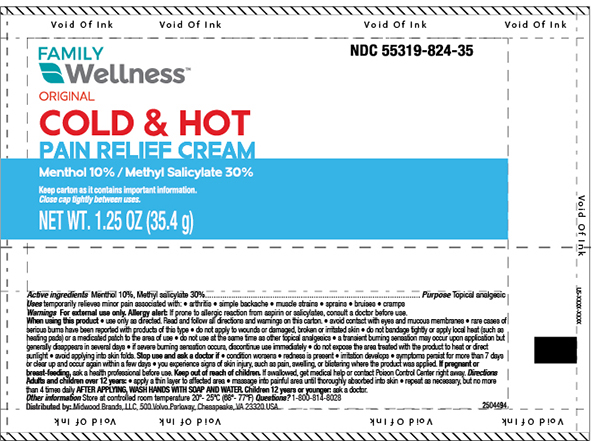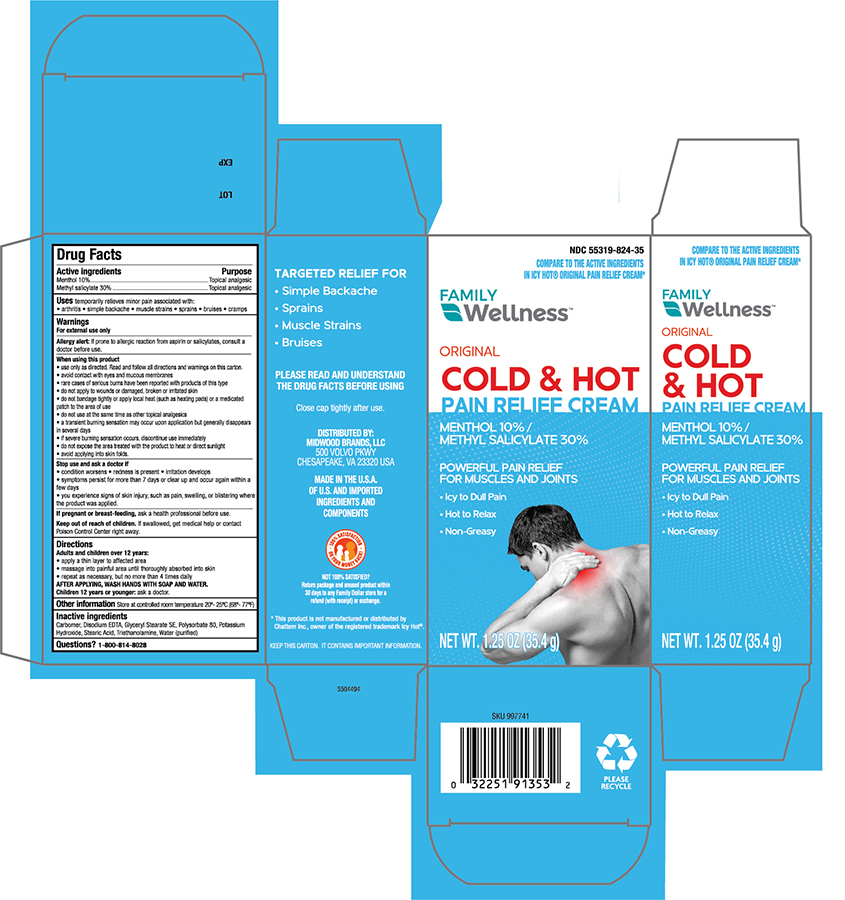 DRUG LABEL: Family Wellness Hot and Cold Pain Relief
NDC: 55319-824 | Form: CREAM
Manufacturer: FAMILY DOLLAR (Family Wellness)
Category: otc | Type: HUMAN OTC DRUG LABEL
Date: 20241121

ACTIVE INGREDIENTS: MENTHOL, UNSPECIFIED FORM 100 mg/1 g; METHYL SALICYLATE 300 mg/1 g
INACTIVE INGREDIENTS: CARBOMER 940; EDETATE DISODIUM ANHYDROUS; GLYCERYL STEARATE SE; POLYSORBATE 80; POTASSIUM HYDROXIDE; STEARIC ACID; TROLAMINE; WATER

Family Wellness Hot and Cold Pain Relief

Active ingredients

Menthol - 10%

Methyl salicylate -30%

Purpose

Topical Analgesic

Topical Analgesic

Uses

For temporary relief of minor aches and pains of muscle and joints associated with;

- simple backaches, arthritis, strains, bruises and sprains

Warning

For external use only

Do not use

- on wounds or damaged skin
- with a heating pad
- on a child under 12 years of age with arthritis-like condiitions

Ask a doctor before use if you have; redness over thre affected area

When using this product

- avoid contact with eyes and mucous membranes
- do not bandage tightly

Stop use and ask a doctor if;

- condition worsens or symptoms persist for more than 7 days
- symptoms clear up and occur again within a few days
- excessive skin irritation occur

KEEP OUT OF REACH OF CHILDREN

Keep this and all drugs out of the reach of children. If swallowed, get medical help or contact a Poison Control Center immediately.

Directions

- Use only as directed

Adults and children 2 years of age and older;

- Apply to affected area not more than 3 to 4 times daily.

Children under 2 years of age; ask a doctor.

Other information

Store at controlled room temperature 20°- 25°C (68° to 77°F)

Principal Display Panel -Tube

Family Wellness NDC 55319-824-35

Cold & Hot Pain Relief Cream

MENTHOL 10%

METHYL SALICYLATE 30%

NET WT 1.25 OZ (35.4g)

Principal Display Panel -Carton

Family Wellness NDC 55319-824-35

Cold & Hot Pain Relief Cream

MENTHOL 10%

METHYL SALICYLATE 30%

NET WT 1.25 OZ (35.4g)